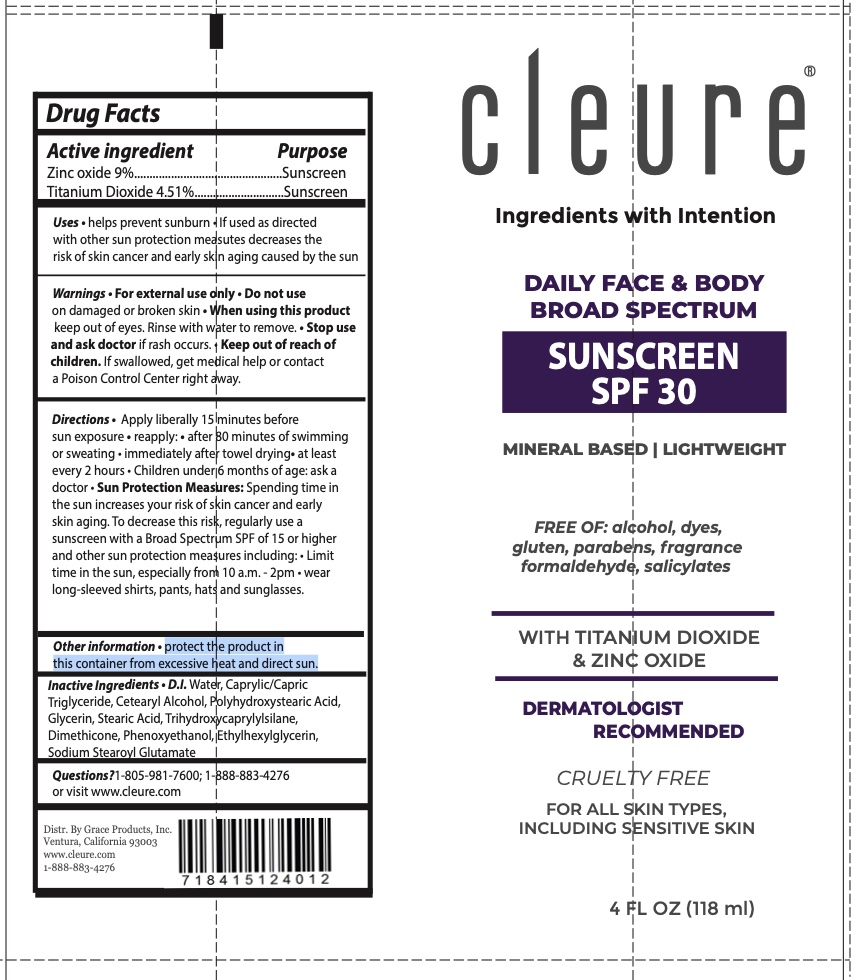 DRUG LABEL: SPF 30 Sunscreen
NDC: 83294-101 | Form: LOTION
Manufacturer: CLEURE
Category: otc | Type: HUMAN OTC DRUG LABEL
Date: 20251229

ACTIVE INGREDIENTS: ZINC OXIDE 9 g/100 mL; TITANIUM DIOXIDE 4.51 g/100 mL
INACTIVE INGREDIENTS: WATER; DIMETHICONE 350; SODIUM STEAROYL GLUTAMATE; STEARETH-21; ALOE VERA LEAF; MEDIUM-CHAIN TRIGLYCERIDES; CETOSTEARYL ALCOHOL; GLYCERIN; PHENOXYETHANOL; XANTHAN GUM; EDETATE DISODIUM; ETHYLHEXYLGLYCERIN; STEARETH-2

Cleure SPF 30 Sunscreen

ACTIVE INGREDIENT

Zinc oxide 9%

Titanium Dioxide 4.51%

PURPOSE

Sunscreen

USES

• helps prevent sunburn • If used as directed
with other sun protection measutes decreases the
risk of skin cancer and early skin aging caused by the sun

WARNINGS

• For external use only • Do not use
on damaged or broken skin • When using this product keep out of eyes. Rinse with water to remove. • Stop use and ask doctor if rash occurs.

Keep out of reach of children. If swallowed, get medical help or contact
a Poison Control Center right away.

DIRECTIONS

Apply liberally 15 minutes before
sun exposure • reapply: • after 80 minutes of swimming or sweating • immediately after towel drying• at least every 2 hours • Children under 6 months of age: ask a doctor • Sun Protection Measures: Spending time in the sun increases your risk of skin cancer and early
skin aging. To decrease this risk, regularly use a sunscreen with a Broad Spectrum SPF of 15 or higher and other sun protection measures including: • Limit time in the sun, especially from 10 a.m. - 2pm • wear long-sleeved shirts, pants, hats and sunglasses.

INACTIVE INGREDIENTS

Water, Caprylic / Capric Triglyceride, Cetearyl Alcohol, STEARETH-2, Glycerin, STEARETH-21, Aloe Vera, Dimethicone, Phenoxyethanol, Sodium Stearoyl Glutamate, Xanthan Gum, Disodium EDTA, Ethylhexylglycerin

STORAGE AND HANDLING

protect the product in this container from excessive heat and direct sun.